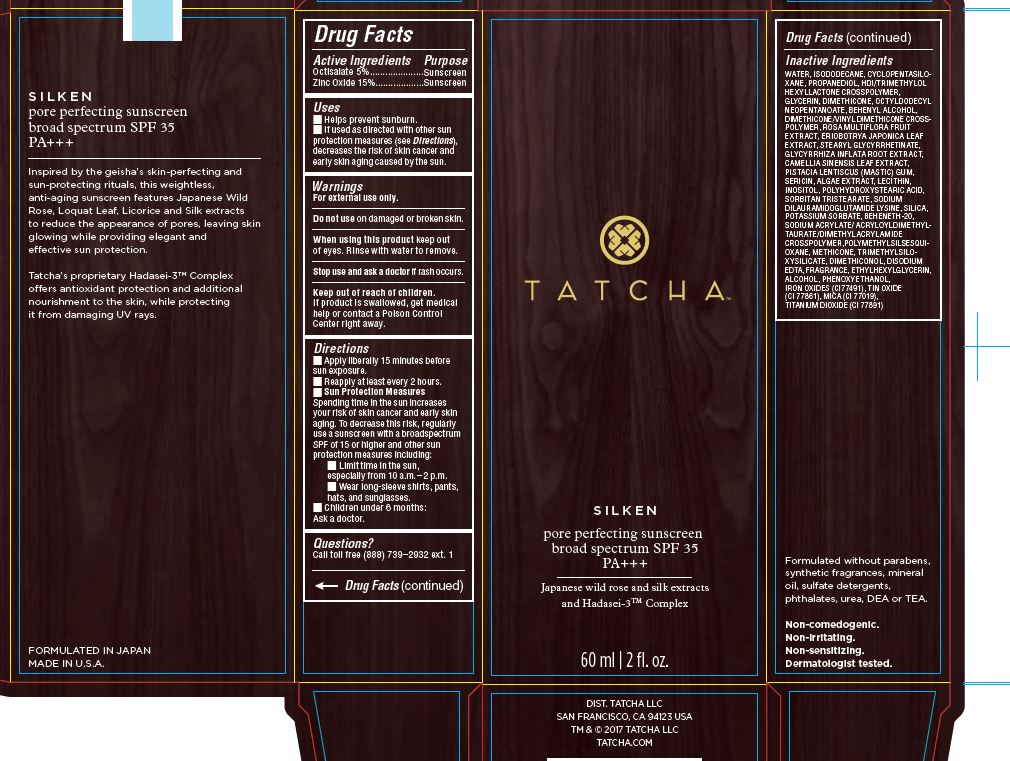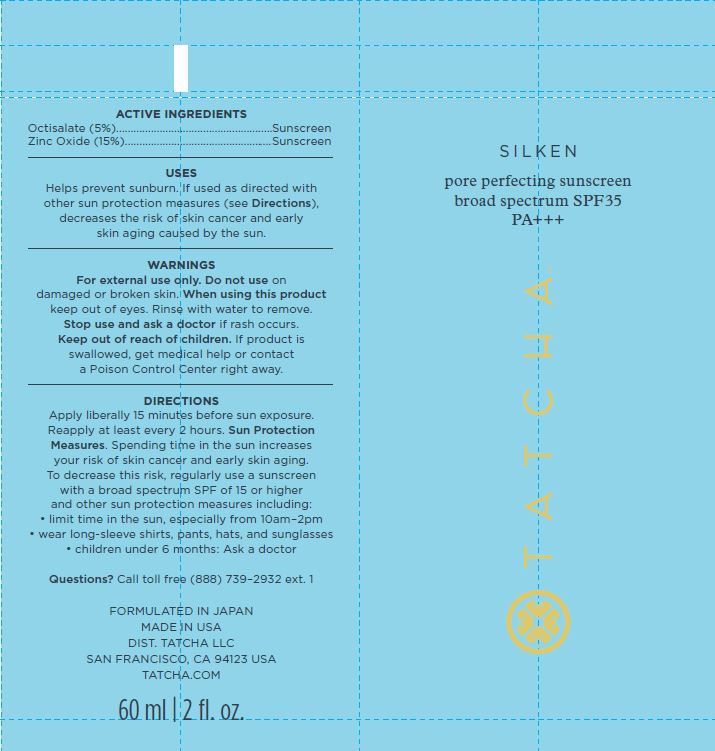 DRUG LABEL: SILKEN pore perfecting sunscreen broad spectrum SPF 35
NDC: 69417-110 | Form: LOTION
Manufacturer: TATCHA INC.
Category: otc | Type: HUMAN OTC DRUG LABEL
Date: 20191230

ACTIVE INGREDIENTS: OCTISALATE 5 g/100 g; ZINC OXIDE 15 1/100 g
INACTIVE INGREDIENTS: WATER; ISODODECANE; DIMETHICONE CROSSPOLYMER (450000 MPA.S AT 12% IN CYCLOPENTASILOXANE); PROPANEDIOL; HEXAMETHYLENE DIISOCYANATE/TRIMETHYLOL HEXYLLACTONE CROSSPOLYMER; GLYCERIN; DIMETHICONE; OCTYLDODECYL NEOPENTANOATE; DIMETHICONE/VINYL DIMETHICONE CROSSPOLYMER (SOFT PARTICLE); ROSA MULTIFLORA FRUIT; ERIOBOTRYA JAPONICA LEAF; STEARYL GLYCYRRHETINATE; GLYCYRRHIZA ECHINATA ROOT; CAMELLIA JAPONICA LEAF; PISTACIA LENTISCUS RESIN; SILK SERICIN; LECITHIN, SOYBEAN; INOSITOL; POLYHYDROXYSTEARIC ACID (2300 MW); SORBITAN TRISTEARATE; POTASSIUM SORBATE; BEHENETH-20; SODIUM ACRYLATE; POLYMETHYLSILSESQUIOXANE (11 MICRONS); TITANIUM DIOXIDE; METHICONE (20 CST); TRIMETHYLSILOXYSILICATE (M/Q 0.6-0.8); DIMETHICONOL (40 CST); BROWN IRON OXIDE; MICA; ETHYLHEXYLGLYCERIN; ALCOHOL; PHENOXYETHANOL

DRUG FACTS

Active Ingredients

Octisalate 5.00%

Zinc Oxide 15.00%

Uses

- Helps prevens sunburn
- If used as direced with other sun protection measures (see Directions), decreases the risk of skin cancer and early skin again caused by the sun.

Warnings

When using this product • keep out of eyes • rinse with water to remove • do not use on damaged or broken skin

Stop use and ask a docor • if rash occurs

Keep out of reach of children. If swalled, get medical help or contact a Poison Control Center right away.

For external use only

Directions

- Apply liberally 15 minutes before sun exposure
- Use water resistant sunscreen if swimming or sweathing
- Reapply at least every 2 hours
- Children under 6 months: ask a doctor
- Sun Protection Measures: Spending time in the sun decreases risk of skin cancer and early again. To decrease this risk, regulaory use a sunscreen with a Broad Spectrum SPF value of 15 or higher and other sun protection measures including: Limit time in the sun especially from 10:00 am - 2:00 pm. Wear long sleeved shirts, pants, hats and sunglasses.

Inactive Ingredients

WATER, ISODODECANE, CYCLOPENTASILOXANE, PROPANEDIOL, HDI/TRIMETHYLOL HEXYLLACTONE CROSSPOLYMER, GLYCERIN, DIMETHICONE, OCTYLDODECYL NEOPENTANOATE, BEHENYL ALCOHOL, DIMETHICONE/VINYL DIMETHICONE CROSSPOLYMER, ROSA MULTIFLORA FRUIT EXTRACT, ERIOBOTRYA JAPONICA LEAF EXTRACT, STEARYL GLYCYRRHETINATE (LICORICE EXTRACT), GLYCYRRHIZA INFLATA (LICORICE) ROOT EXTRACT, CAMELLIA SINENSIS (GREEN TEA) LEAF EXTRACT, PISTACIA LENTISCUS (MASTIC) GUM, SERICIN (SILK EXTRACT), ALGAE EXTRACT, LECITHIN, INOSITOL (RICE EXTRACT), POLYHYDROXYSTEARIC ACID, SORBITAN TRISTEARATE, SODIUM DILAURAMIDOGLUTAMIDE LYSINE, SILICA, POTASSIUM SORBATE, BEHENETH-20, SODIUM ACRYLATE/ACRYLOYLDIMETHYLTAURATE/DIMETHYLACRYLAMIDE CROSSPOLYMER, POLYMETHYLSILSESQUIOXANE, TITANIUM DIOXIDE, METHICONE, TRIMETHYLSILOXYSILICATE, DIMETHICONOL, DISODIUM EDTA, IRON OXIDES (CI77491), TIN OXIDE, MICA, FRAGRANCE (NATURAL), ETHYLHEXYLGLYCERIN, ALCOHOL, PHENOXYETHANOL.

Other Information

- Protect this product form excessive heat and direct sun.

PACKAGE LABEL

TATCHA

SILKEN

pore perfecting sunscreen

broad spectrum SPF 35

PA +++

Japanese wild rose and silk extracts

and Hadasei-3TM Complex

60 ml| 2 fl. oz.